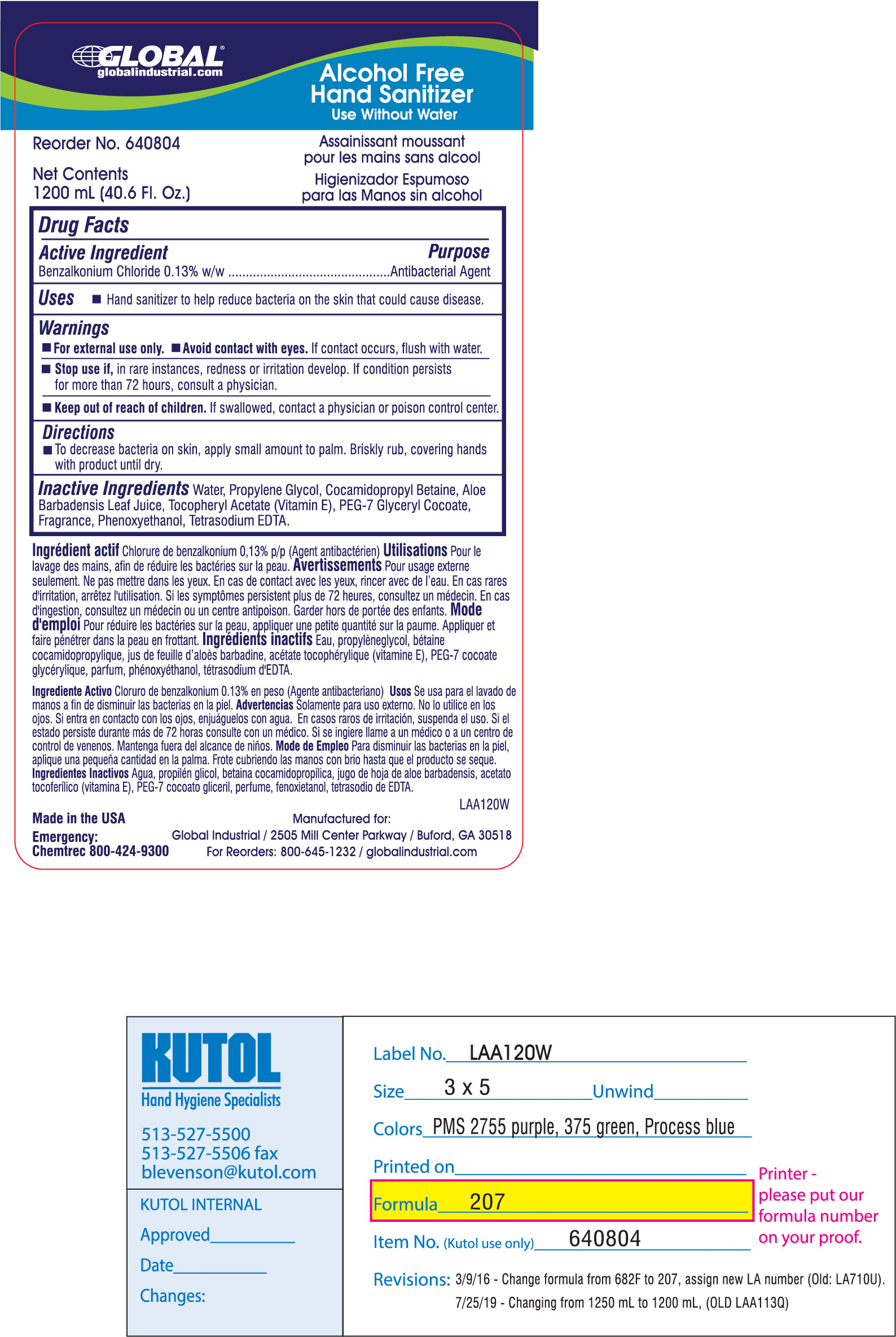 DRUG LABEL: Foaming Instant Hand Sanitizer
NDC: 78641-207 | Form: SOLUTION
Manufacturer: Global Equipment Company
Category: otc | Type: HUMAN OTC DRUG LABEL
Date: 20230824

ACTIVE INGREDIENTS: BENZALKONIUM CHLORIDE 0.013 mg/1 mL
INACTIVE INGREDIENTS: COCAMIDOPROPYL BETAINE; PEG-7 GLYCERYL COCOATE; PHENOXYETHANOL; EDETATE SODIUM; PROPYLENE GLYCOL 1,2-DISTEARATE; .ALPHA.-TOCOPHEROL ACETATE, D-; ALOE VERA LEAF; WATER

Global Equipment F207

Active Ingredient Benzalkonium Chloride 0.13% w/w

Purpose Antibacterial Agent

INDICATIONS AND USAGE

Uses Hand sanitizer to help reduce bacteria on the skin that could cause disease.

Warnings

For external use only. Avoid contact with eyes. If contact occurs, flush with water.

Stop use if, in rare instances, redness or irritation develop. If condition persists for more than 72 hours, consult a physician.

Directions

To decrease bacteria on skin, apply a small amount to palm. Briskly rub, covering hands with product until dry.

Keep out of reach of children. If swallowed, contact a poison control center.

Inactive Ingredients

Water, Propylene Glycol, Cocamidopropyl Betaine, Aloe Barbadensis Leaf Juice, Tocopheryl Acetate, PEG-7 Glyceryl Cocoate, Fragrance, Phenoxyethanol, Tetrasodium EDTA.

Package Label